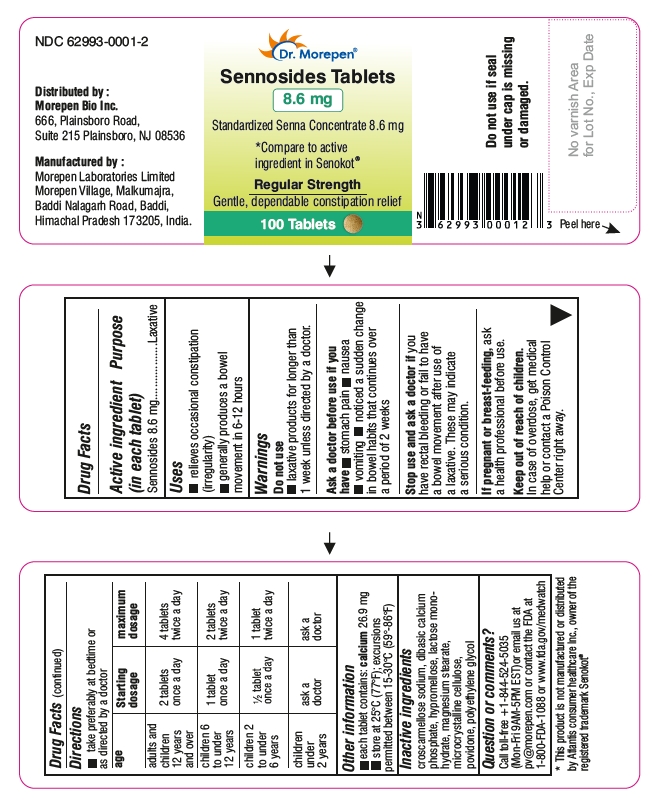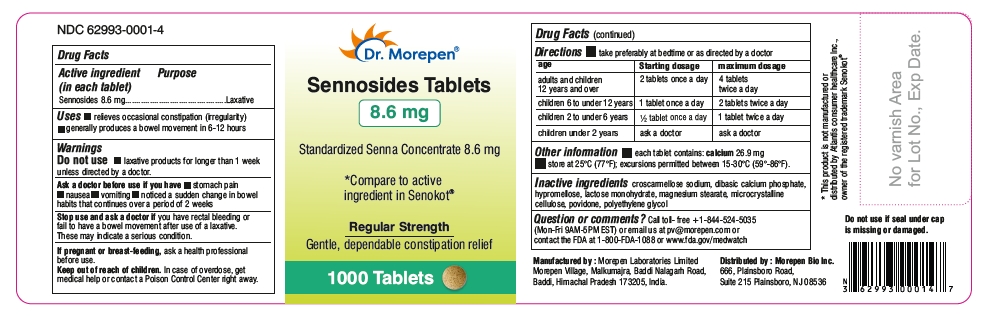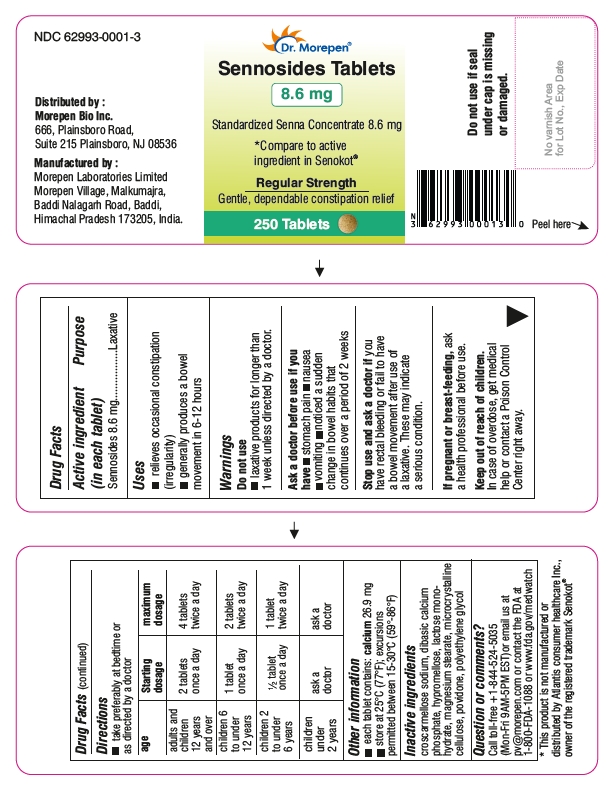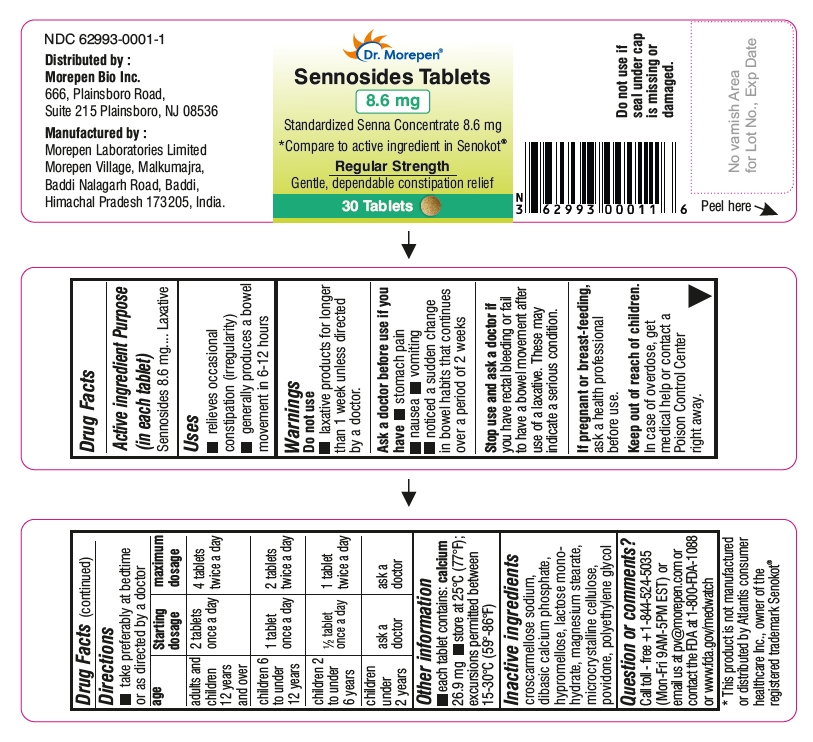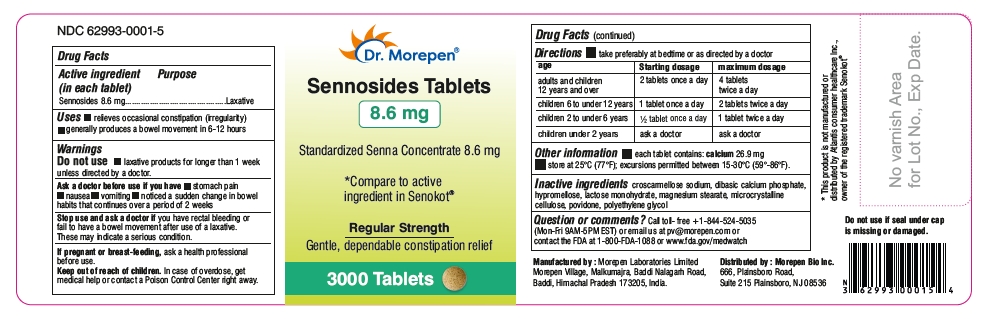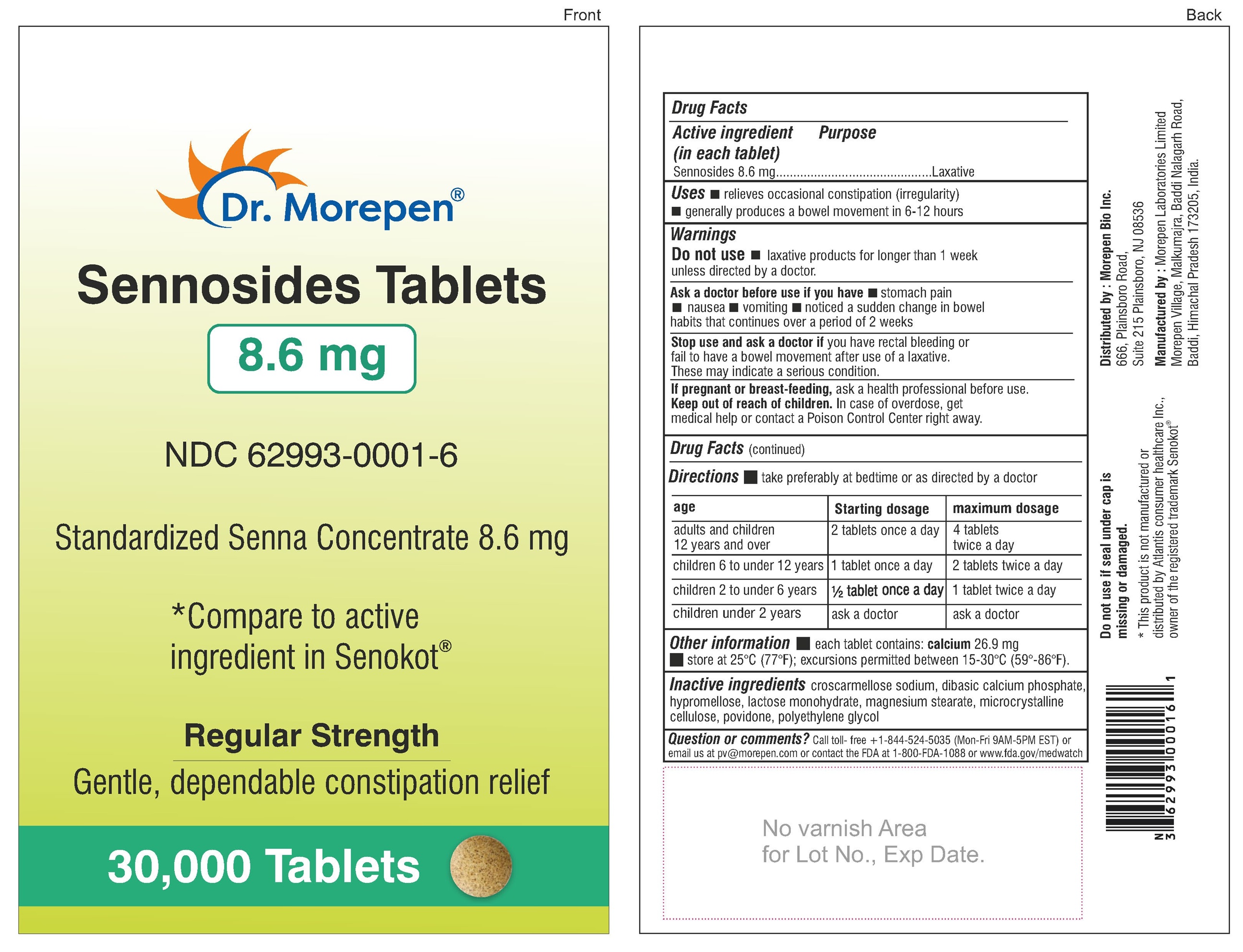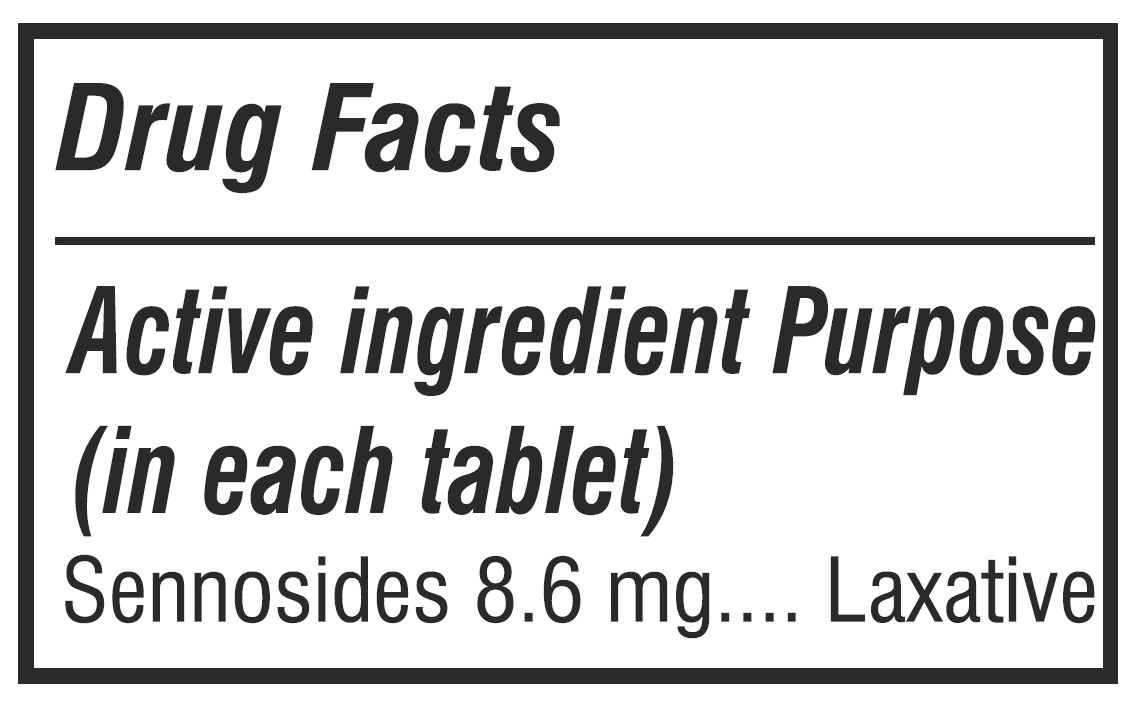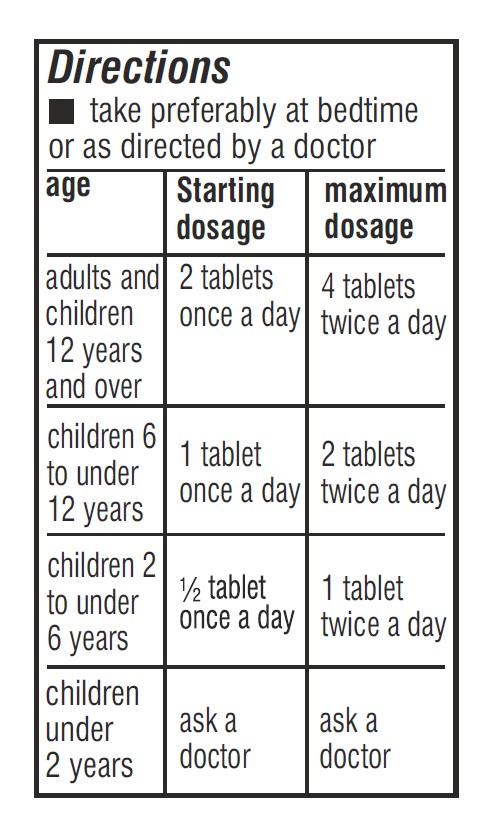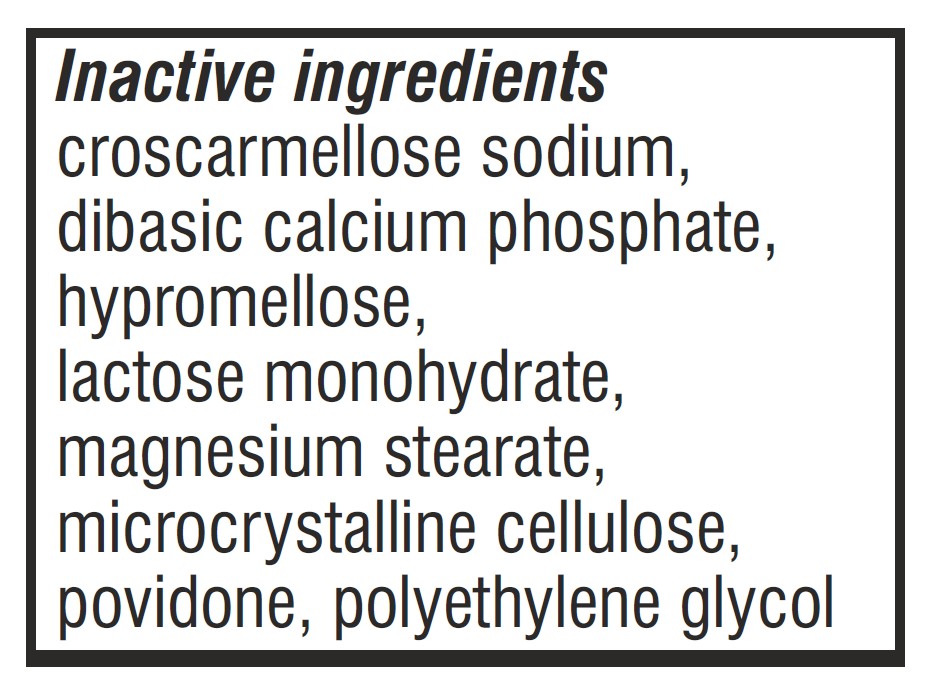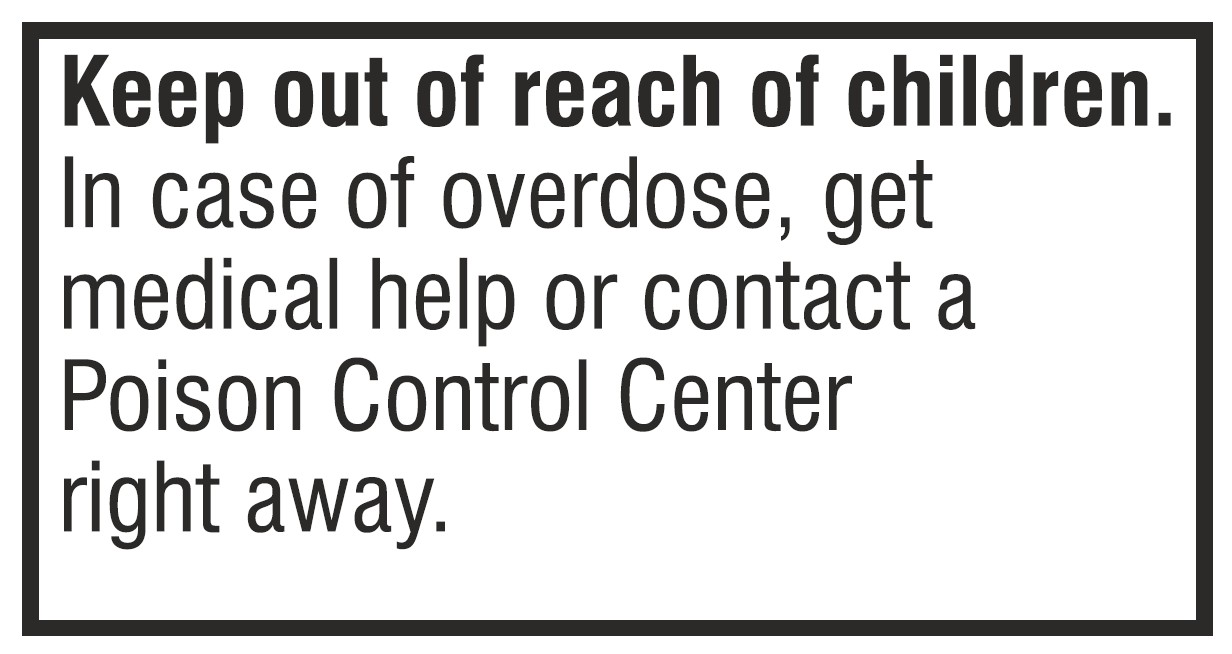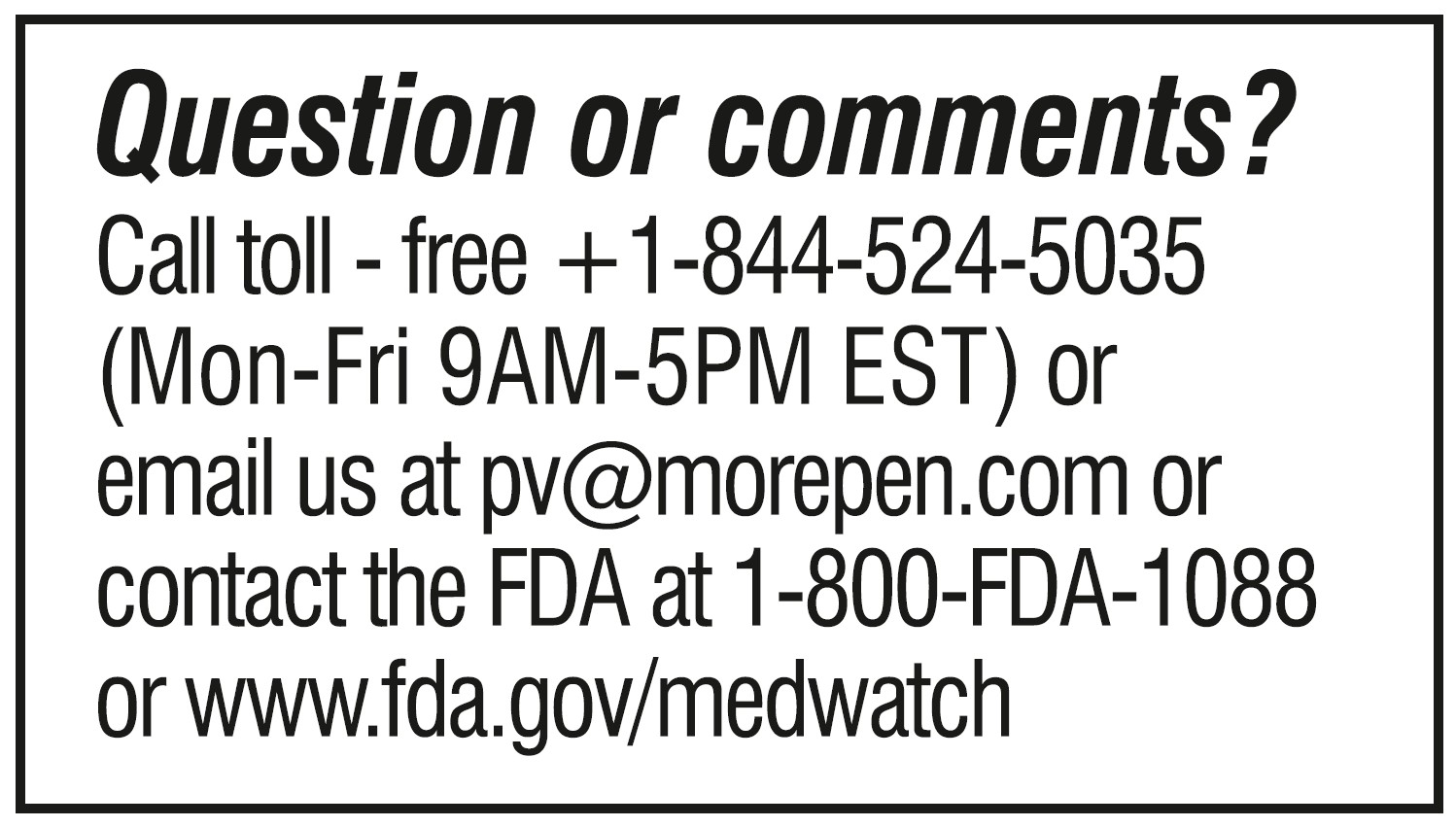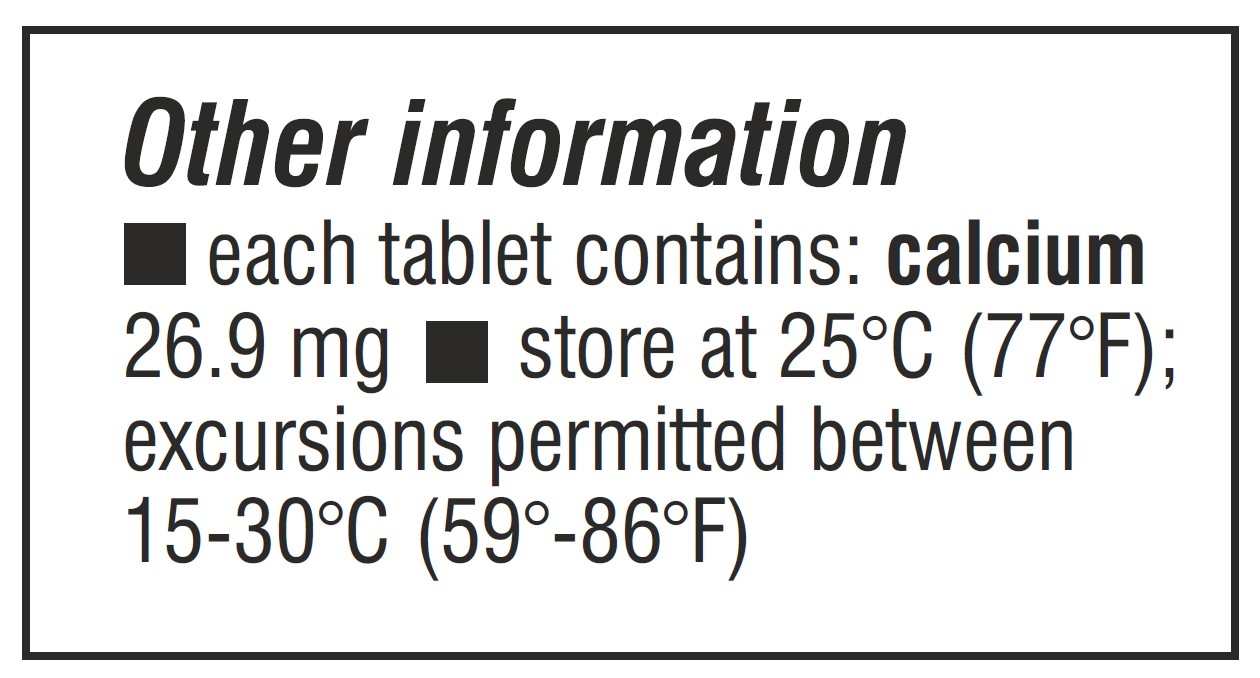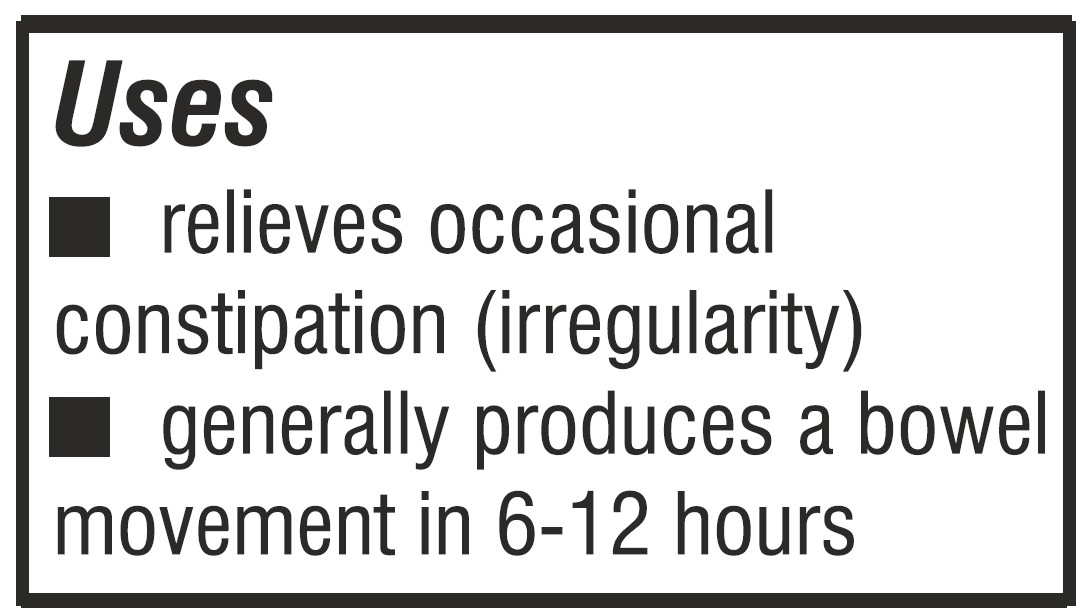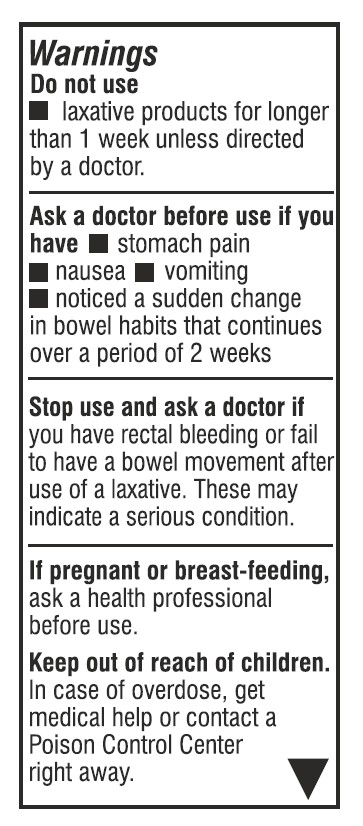 DRUG LABEL: Sennosides
NDC: 62993-0001 | Form: TABLET
Manufacturer: Morepen Laboratories Limited
Category: otc | Type: HUMAN OTC DRUG LABEL
Date: 20251216

ACTIVE INGREDIENTS: SENNOSIDES 8.6 mg/1 1
INACTIVE INGREDIENTS: CALCIUM PHOSPHATE, DIBASIC, ANHYDROUS; MAGNESIUM STEARATE; MICROCRYSTALLINE CELLULOSE 102; POVIDONE K30; HYPROMELLOSE 2910 (3 MPA.S); POLYETHYLENE GLYCOL 3350; CROSCARMELLOSE SODIUM; LACTOSE MONOHYDRATE

Sennosides Tablet 8.6mg